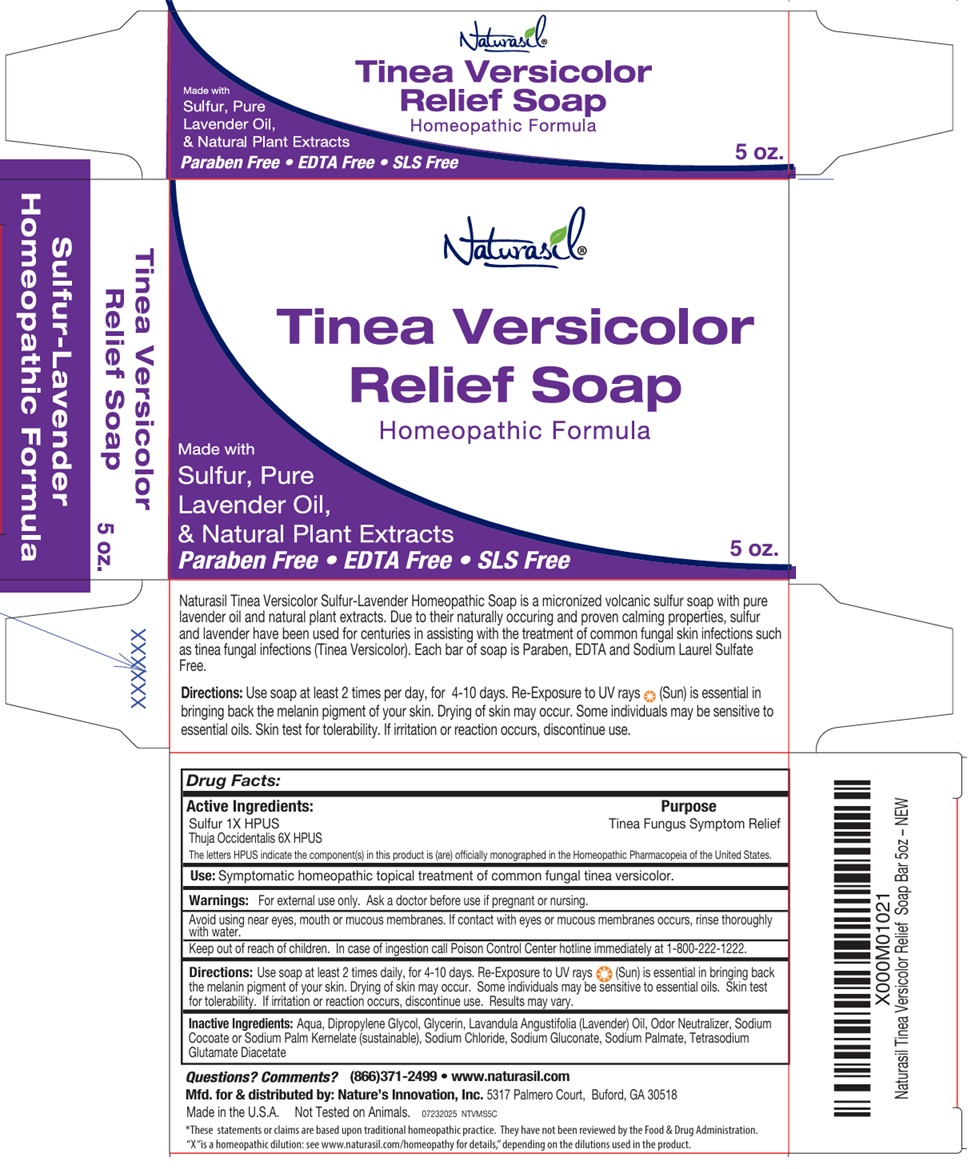 DRUG LABEL: Naturasil
NDC: 10893-620 | Form: SOAP
Manufacturer: Nature's Innovation, Inc.
Category: homeopathic | Type: HUMAN OTC DRUG LABEL
Date: 20251007

ACTIVE INGREDIENTS: SULFUR 1 [hp_X]/1 g; THUJA OCCIDENTALIS LEAFY TWIG 6 [hp_X]/1 g
INACTIVE INGREDIENTS: WATER; DIPROPYLENE GLYCOL; GLYCERIN; LAVENDER OIL; SODIUM COCOATE; SODIUM PALM KERNELATE; SODIUM CHLORIDE; SODIUM GLUCONATE; SODIUM PALMATE; TETRASODIUM GLUTAMATE DIACETATE

Tinea Versicolor Soap

Active Ingredients:

Sulfur 1X HPUS
Thuja Occidentalis 6X HPUS.

The letters HPUS indicate the component(s) in this product is (are) officially monographed in the Homeopathic Pharmacopeia of the United States.

Purpose

Tinea Fungus Symptom Relief

Use:

Symptomatic homeopathic topical treatment of common fungal tinea versicolor.

Warnings:

For external use only. Ask a doctor before use if pregnant or nursing.

Avoid using near eyes, mouth or mucous membranes. If contact with eyes or mucous membranes occurs, rinse thoroughly with water.

Keep out of reach of children. In case of ingestion, call Poison Control Center hotline immediately at 1-800-222-1222.

Directions:

Use soap at least 2 times daily, for 4-10 days. Re-Exposure to UV rays (Sun) is essential in bringing back the melanin pigment of your skin. Drying of skin may occur. Some individuals may be sensitive to essential oils. Skin test for tolerability. If irritation or reaction occurs, discontinue use. Results may vary.

Inactive Ingredients:

Aqua, Dipropylene Glycol, Glycerin, Lavandula Angustifolia (Lavender) Oil, Odor Neutralizer, Sodium Cocoate or Sodium Palm Kernelate (sustainable), Sodium Chloride, Sodium Gluconate, Sodium Palmate, Tetrasodium Glutamate Diacetate

Questions? Comments?

(866)371-2499 • www.naturasil.com

Relief Soap

Homeopathic Formula

Made with Sulfur, Pure Lavender Oil, & Natural Plant Extracts

Paraben Free • EDTA Free • SLS Free

Naturasil Tinea Versicolor Sulfur-Lavender Homeopathic Soap is a micronized volcanic sulfur soap with pure lavender oil and natural plant extracts. Due to their naturally occurring and proven calming properties, sulfur and lavender have been used for centuries in assisting with the treatment of common fungal skin infections such as tinea fungal infections (Tinea Versicolor). Each bar of soap is Paraben, EDTA and Sodium Laurel Sulfate Free.

Mfd. for & distributed by: Nature’s Innovation, Inc. 5317 Palmero Court, Buford, GA 30518

Made in the U.S.A. Not Tested on Animals.

*These statements or claims are based upon traditional homeopathic practice. They have not been reviewed by the Food & Drug Administration. “X“ is a homeopathic dilution: see www.naturasil.com/homeopathy for details,” depending on the dilutions used in the product.